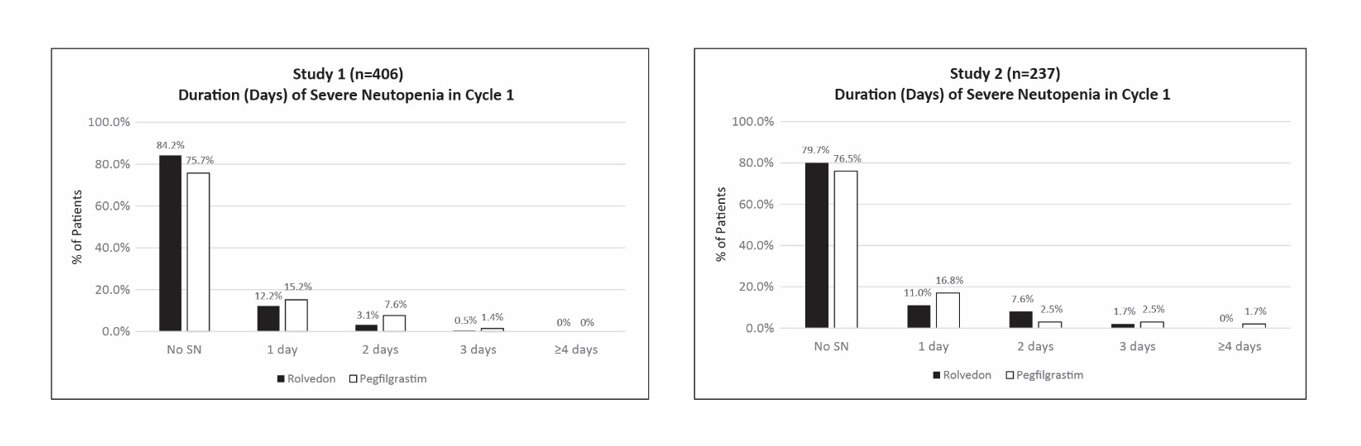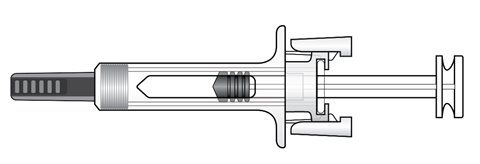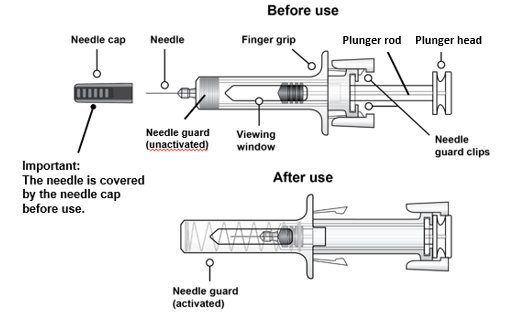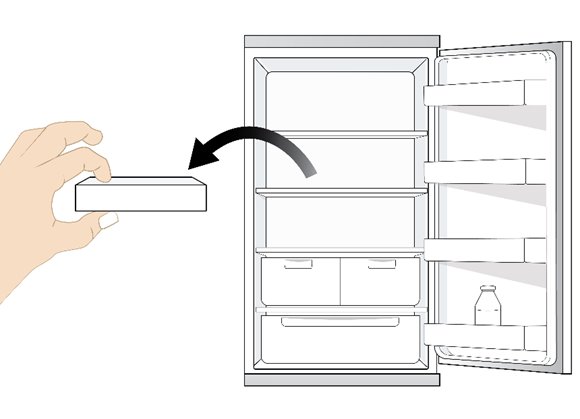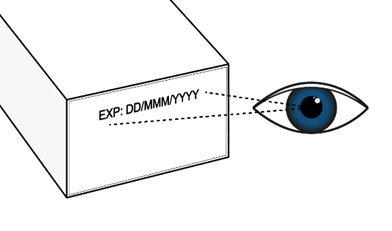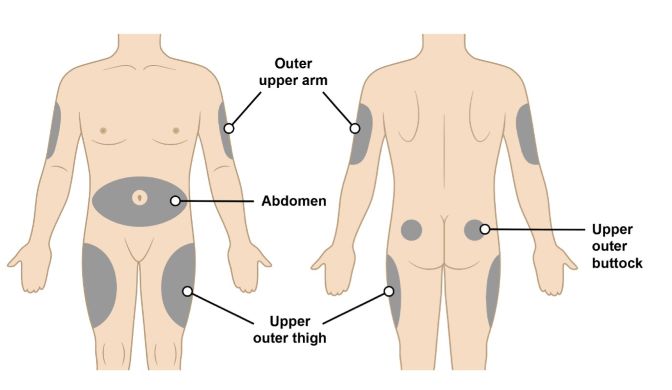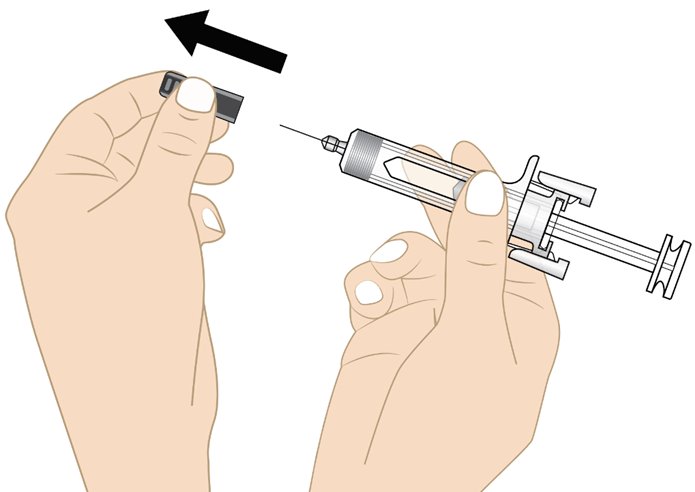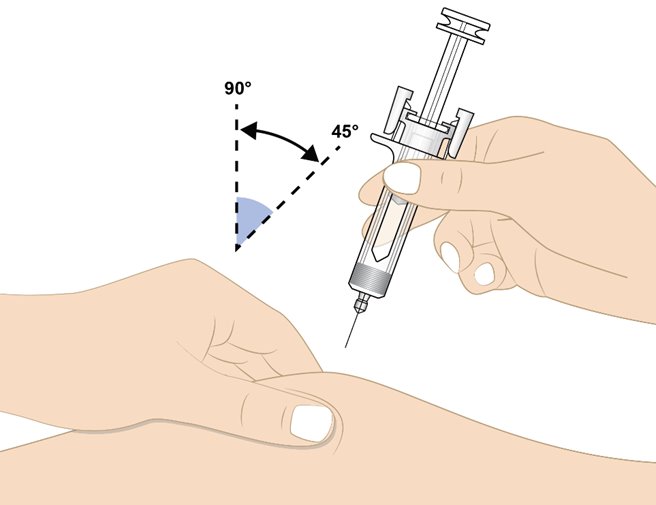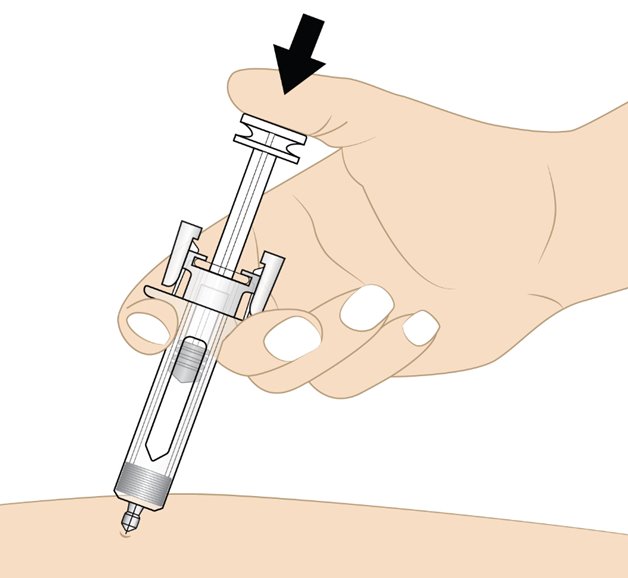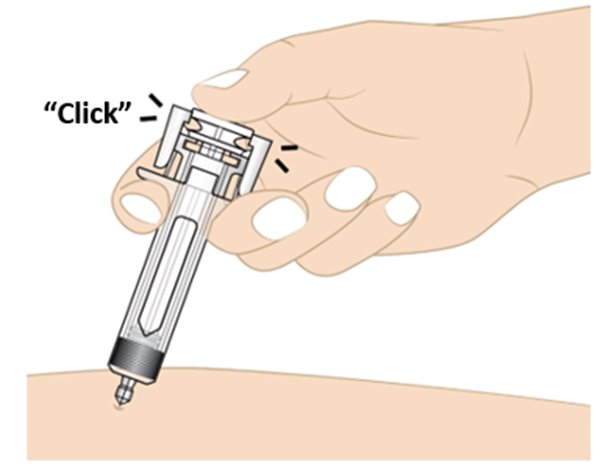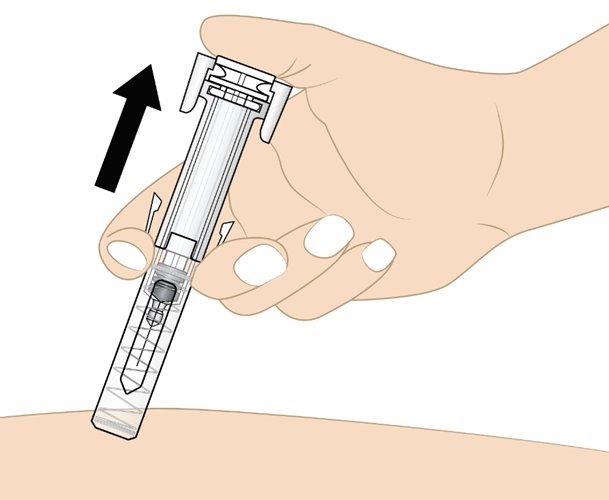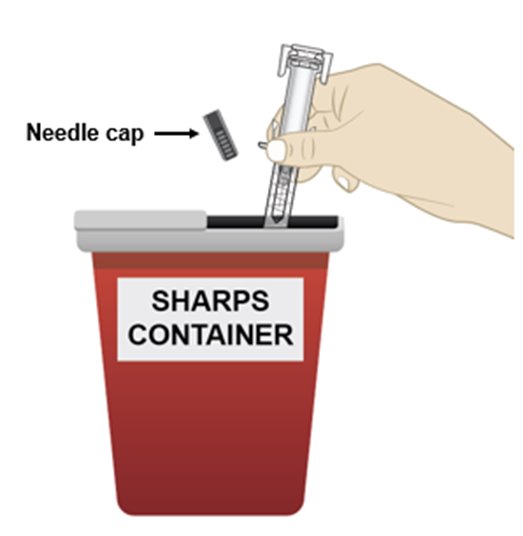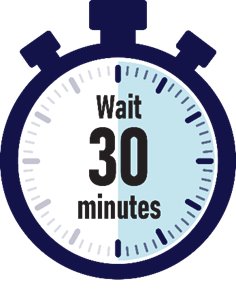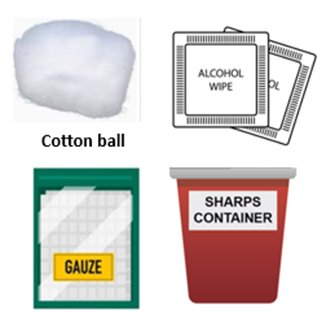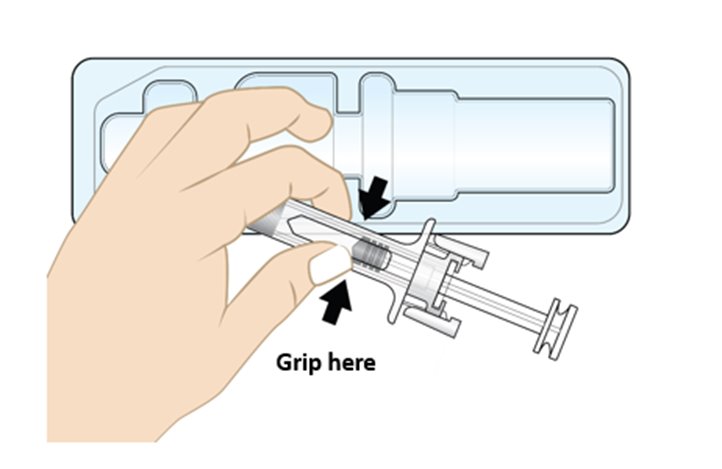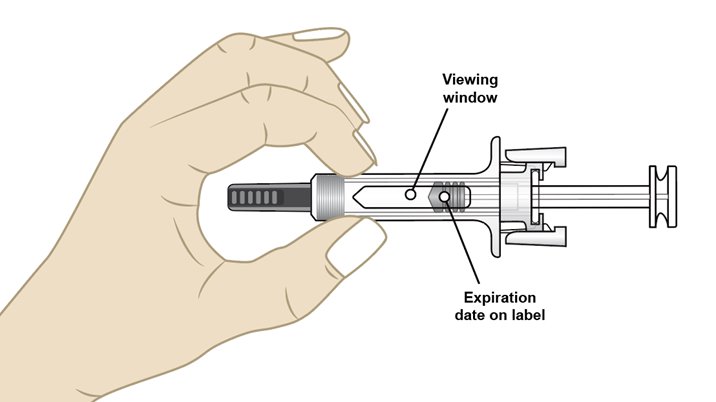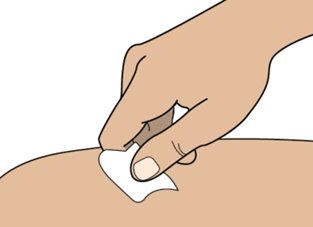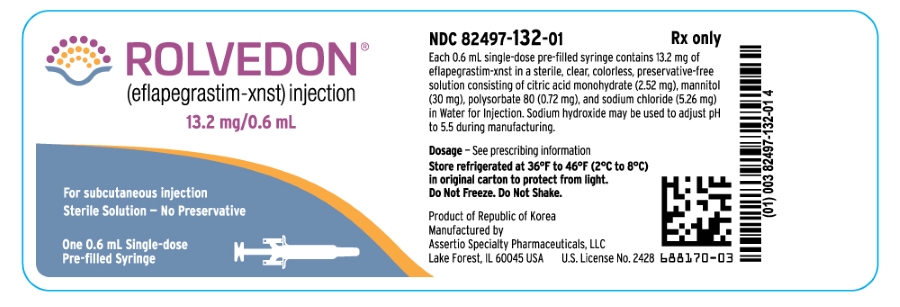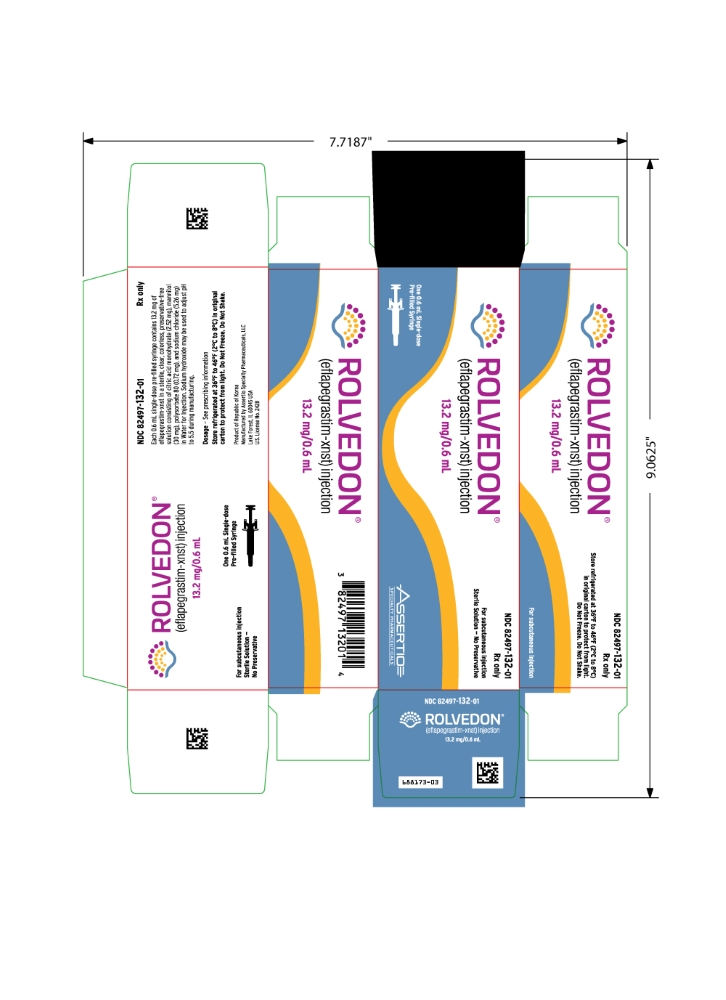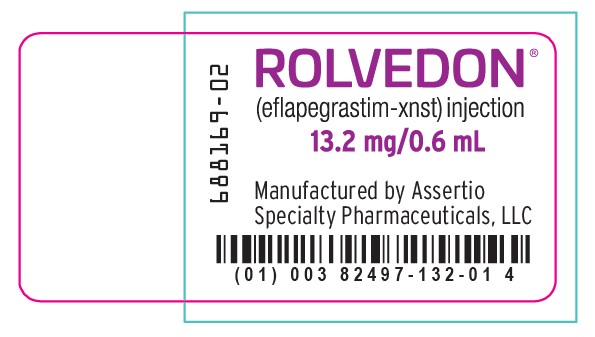 DRUG LABEL: Rolvedon
NDC: 82497-132 | Form: INJECTION, SOLUTION
Manufacturer: Assertio Specialty Pharmaceuticals, LLC
Category: prescription | Type: HUMAN PRESCRIPTION DRUG LABEL
Date: 20260211

ACTIVE INGREDIENTS: EFLAPEGRASTIM 13.2 mg/0.6 mL

HIGHLIGHTS OF PRESCRIBING INFORMATION

These highlights do not include all the information needed to use ROLVEDON® safely and effectively. See full prescribing information for ROLVEDON.
ROLVEDON® (eflapegrastim-xnst) injection, for subcutaneous use
Initial U.S. Approval: 2022

RECENT MAJOR CHANGES

Dosage and Administration, Administration (2.2) 07/2025

1 INDICATIONS AND USAGE

Rolvedon is a leukocyte growth factor indicated to decrease the incidence of infection, as manifested by febrile neutropenia, in adult patients with non-myeloid malignancies receiving myelosuppressive anti-cancer drugs associated with clinically significant incidence of febrile neutropenia. (1)

Limitations of Use

Rolvedon is not indicated for the mobilization of peripheral blood progenitor cells for hematopoietic stem cell transplantation. (1)

2 DOSAGE AND ADMINISTRATION

- Recommended Dose: 13.2 mg administered subcutaneously once per chemotherapy cycle. (2.1)
- Administer approximately 24 hours after cytotoxic chemotherapy. Do not administer within the period from 14 days before to 24 hours after administration of cytotoxic chemotherapy. (2.1)

3 DOSAGE FORMS AND STRENGTHS

Injection: 13.2 mg/0.6 mL solution in a single-dose prefilled syringe. (3)

4 CONTRAINDICATIONS

Patients with a history of serious allergic reactions to human granulocyte colony-stimulating factors such as eflapegrastim, pegfilgrastim or filgrastim products. (4)

5 WARNINGS AND PRECAUTIONS

- Fatal splenic rupture: Evaluate patients who report left upper abdominal or shoulder pain for an enlarged spleen or splenic rupture. (5.1)
- Acute respiratory distress syndrome (ARDS): Evaluate patients who develop fever, lung infiltrates, or respiratory distress. Discontinue Rolvedon in patients with ARDS. (5.2)
- Serious allergic reactions, including anaphylaxis: Permanently discontinue Rolvedon in patients with serious allergic reactions. (5.3)
- Sickle Cell Crisis in Patients with Sickle Cell Disorders: Discontinue Rolvedon if sickle cell crisis occurs. (5.4)
- Glomerulonephritis: Evaluate and consider dose-reduction or interruption of Rolvedon if causality is likely. (5.5)
- Leukocytosis: Monitor complete blood count (CBC) during Rolvedon therapy. (5.6)
- Thrombocytopenia: Monitor platelet counts. (5.7)
- Myelodysplastic Syndrome (MDS) and Acute Myeloid Leukemia (AML): Monitor patients with breast and lung cancer using Rolvedon in conjunction with chemotherapy and/or radiotherapy for signs and symptoms of MDS/AML. (5.10)

6 ADVERSE REACTIONS

The most common adverse reactions (≥20%) are fatigue, nausea, diarrhea, bone pain, headache, pyrexia, anemia, rash, myalgia, arthralgia, and back pain. (6.1)

To report SUSPECTED ADVERSE REACTIONS, contact 1-800-518-1084 or FDA at 1-800-FDA-1088 or www.fda.gov/medwatch

FULL PRESCRIBING INFORMATION

1 INDICATIONS AND USAGE

Rolvedon is indicated to decrease the incidence of infection, as manifested by febrile neutropenia, in adult patients with non-myeloid malignancies receiving myelosuppressive anti-cancer drugs associated with clinically significant incidence of febrile neutropenia.

Limitations of Use

Rolvedon is not indicated for the mobilization of peripheral blood progenitor cells for hematopoietic stem cell transplantation.

2 DOSAGE AND ADMINISTRATION

2.1 Recommended Dosage

The recommended dosage of Rolvedon is a single subcutaneous injection of 13.2 mg administered once per chemotherapy cycle. Administer approximately 24 hours after cytotoxic chemotherapy. Do not administer within the period from 14 days before to 24 hours after administration of cytotoxic chemotherapy.

2.2 Administration

Rolvedon is administered subcutaneously via a single-dose prefilled syringe.

Prior to use‚ take the carton out of the refrigerator and place the sealed blister tray on a clean flat surface for a minimum of 30 minutes to allow the product to reach room temperature. Do not warm up the prefilled syringe in any other way. Discard any prefilled syringe left at room temperature for greater than 72 hours. Do not shake. If Rolvedon is accidentally frozen, do not use. Remove the tray from box and carefully remove the prefilled syringe from the tray. If you drop the prefilled syringe onto a hard surface, do not use it. Use a new syringe for the injection.

Parenteral drug products should be inspected visually for particulate matter and discoloration prior to administration, whenever solution and container permit. Do not administer Rolvedon if discoloration or particulates are observed.

Administer the entire contents of the prefilled syringe.

If the patient or caregiver misses a dose of Rolvedon, instruct them to contact their healthcare provider.

The Rolvedon prefilled syringe does not bear graduation marks and is intended only to deliver the entire contents of the syringe (13.2 mg/0.6 mL) for direct administration.

Not made with natural rubber latex.

3 DOSAGE FORMS AND STRENGTHS

Injection: 13.2 mg/0.6 mL as a clear, colorless, preservative-free solution in a single-dose prefilled syringe.

4 CONTRAINDICATIONS

Rolvedon is contraindicated in patients with a history of serious allergic reactions to eflapegrastim, pegfilgrastim, or filgrastim products. Reactions may include anaphylaxis [see Warnings and Precautions (5.3)].

5 WARNINGS AND PRECAUTIONS

5.1 Splenic Rupture

Splenic rupture, including fatal cases, can occur following the administration of recombinant human granulocyte colony-stimulating factor (rhG-CSF) products, such as Rolvedon. Evaluate for an enlarged spleen or splenic rupture in patients who report left upper abdominal or shoulder pain after receiving Rolvedon.

5.2 Acute Respiratory Distress Syndrome

Acute respiratory distress syndrome (ARDS) can occur in patients receiving rhG-CSF products, such as Rolvedon. Evaluate patients who develop fever and lung infiltrates or respiratory distress after receiving Rolvedon for ARDS. Discontinue Rolvedon in patients with ARDS.

5.3 Serious Allergic Reactions

Serious allergic reactions, including anaphylaxis, can occur in patients receiving rhG-CSF products, such as Rolvedon. Permanently discontinue Rolvedon in patients with serious allergic reactions. Rolvedon is contraindicated in patients with a history of serious allergic reactions to eflapegrastim, pegfilgrastim, or filgrastim products [see Contraindications (4)].

5.4 Sickle Cell Crisis in Patients with Sickle Cell Disorders

Severe and sometimes fatal sickle cell crises can occur in patients with sickle cell disorders receiving rhG-CSF products, such as Rolvedon. Discontinue Rolvedon if sickle cell crisis occurs.

5.5 Glomerulonephritis

Glomerulonephritis has occurred in patients receiving rhG-CSF products. The diagnoses were based upon azotemia, hematuria (microscopic and macroscopic), proteinuria, and renal biopsy. Generally, events of glomerulonephritis resolved after dose-reduction or discontinuation of rhG-CSF. If glomerulonephritis is suspected, evaluate for cause. If causality is likely, consider dose-reduction or interruption of Rolvedon.

5.6 Leukocytosis

White blood cell (WBC) counts of 100 x 10^9/L or greater have been observed in patients receiving rhG-CSF products. Monitor complete blood count (CBC) during Rolvedon therapy. Discontinue Rolvedon treatment if WBC count of 100 x 10^9/L or greater occurs.

5.7 Thrombocytopenia

Thrombocytopenia has been reported in patients receiving rhG-CSF products. Monitor platelet counts.

5.8 Capillary Leak Syndrome

Capillary leak syndrome has been reported after administration of rhG-CSF products and is characterized by hypotension, hypoalbuminemia, edema and hemoconcentration. Episodes vary in frequency and severity, and may be life-threatening if treatment is delayed. Patients who develop symptoms of capillary leak syndrome should be closely monitored and receive standard symptomatic treatment, which may include a need for intensive care.

5.9 Potential for Tumor Growth Stimulatory Effects on Malignant Cells

The granulocyte colony-stimulating factor (G-CSF) receptor through which Rolvedon acts has been found on tumor cell lines. The possibility that Rolvedon acts as a growth factor for any tumor type, including myeloid malignancies and myelodysplasia, diseases for which Rolvedon is not approved, cannot be excluded.

5.10 Myelodysplastic Syndrome (MDS) and Acute Myeloid Leukemia (AML) in Patients with Breast and Lung Cancer

MDS and AML have been associated with the use of rhG-CSF products in conjunction with chemotherapy and/or radiotherapy in patients with breast and lung cancer. Monitor patients for signs and symptoms of MDS/AML in these settings.

5.11 Aortitis

Aortitis has been reported in patients receiving rhG-CSF products. It may occur as early as the first week after start of therapy. Manifestations may include generalized signs and symptoms such as fever, abdominal pain, malaise, back pain, and increased inflammatory markers (e.g., c-reactive protein and white blood cell count). Consider aortitis in patients who develop these signs and symptoms without known etiology. Discontinue Rolvedon if aortitis is suspected.

5.12 Nuclear Imaging

Increased hematopoietic activity of the bone marrow in response to growth factor therapy has been associated with transient positive bone imaging findings. This should be considered when interpreting bone imaging results.

6 ADVERSE REACTIONS

The following clinically significant adverse reactions are discussed in greater detail in other sections of the labeling:

- Splenic rupture [see Warnings and Precautions (5.1)]
- Acute respiratory distress syndrome [see Warnings and Precautions (5.2)]
- Serious allergic reactions [see Warnings and Precautions (5.3)]
- Sickle cell crisis in patients with sickle cell disorders [see Warnings and Precautions (5.4)]
- Glomerulonephritis [see Warnings and Precautions (5.5)]
- Leukocytosis [see Warnings and Precautions (5.6)]
- Thrombocytopenia [see Warnings and Precautions (5.7)]
- Capillary leak syndrome [see Warnings and Precautions (5.8)]
- Potential for tumor growth stimulatory effects on malignant cells [see Warnings and Precautions (5.9)]
- Myelodysplastic Syndrome (MDS) and Acute Myeloid Leukemia (AML) in Patients with Breast and Lung Cancer [see Warnings and Precautions (5.10)]
- Aortitis [see Warnings and Precautions (5.11)]
- Nuclear Imaging [see Warnings and Precautions (5.12)]

6.1 Clinical Trials Experience

Because clinical trials are conducted under widely varying conditions, adverse reaction rates observed in the clinical trials of a drug cannot be directly compared to rates in the clinical trials of another drug and may not reflect the rates observed in clinical practice.

The safety of Rolvedon was evaluated in Study 1 and Study 2 [see Clinical Studies (14)]. Patients with early-stage breast cancer received Rolvedon 13.2 mg by subcutaneous injection (n=314) or pegfilgrastim 6 mg by subcutaneous injection (n=326) on Day 2 of each cycle after docetaxel 75 mg/m^2 and cyclophosphamide 600 mg/m^2 (TC) chemotherapy.

Among patients receiving Rolvedon, a total of 272 patients received four 21-day treatment cycles. The most common adverse reactions (≥20%) were fatigue, nausea, diarrhea, bone pain, headache, pyrexia, anemia, rash, myalgia, arthralgia, and back pain. Table 1 summarizes the adverse reactions that occurred in Studies 1 and 2.

Table 1. Common Adverse Reactions with a Frequency of ≥10% Through Week 14 in Patients with Early-Stage Breast Cancer in Study 1 and Study 2
Adverse Reaction | Rolvedon (N = 314) % | Pegfilgrastim** (N=326) %
Fatigue * | 181 (58%) | 192 (59%)
Nausea | 162 (52%) | 166 (51%)
Diarrhea | 125 (40%) | 126 (39%)
Bone pain | 119 (38%) | 121 (37%)
Headache* | 92 (29%) | 90 (28%)
Pyrexia * | 87 (28%) | 84 (26%)
Anemia* | 77 (25%) | 52 (16%)
Rash* | 77 (25%) | 99 (30%)
Myalgia | 69 (22%) | 49 (15%)
Arthralgia | 66 (21%) | 48 (15%)
Back pain* | 63 (20%) | 55 (17%)
Decreased appetite | 61 (19%) | 50 (15%)
Peripheral edema* | 57 (18%) | 53 (16%)
Abdominal pain* | 53 (17%) | 67 (21%)
Dizziness * | 50 (16%) | 38 (12%)
Dyspnea* | 49 (16%) | 44 (13%)
Cough* | 48 (15%) | 51 (16%)
Thrombocytopenia* | 44 (14%) | 17 (5%)
Pain | 37 (12%) | 42 (13%)
Pain in extremity | 36 (11%) | 42 (13%)
Local administration reactions* | 34 (11%) | 27 (8%)
Flushing | 32 (10%) | 27 (8%)
*Grouped Terms
**Study 1 and Study 2 were not designed to evaluate meaningful comparisons of the incidence of adverse reactions in the Rolvedon and the pegfilgrastim treatment groups.

Permanent discontinuation due to an adverse reaction occurred in 4% of patients who received Rolvedon. The adverse reaction requiring permanent discontinuation in 3 patients who received Rolvedon was rash.

8 USE IN SPECIFIC POPULATIONS

8.1 Pregnancy

Risk Summary

There are no available data on Rolvedon use in pregnant women; however, data from published studies with use of other recombinant human granulocyte colony-stimulating factor (rhG-CSF) products in pregnant women have not identified any drug-associated risk of major birth defects, miscarriage or adverse maternal or fetal outcomes.

Animal reproduction studies were conducted in rats and rabbits. In rats, eflapegrastim-xnst did not adversely affect embryofetal and/or postnatal development when administered from organogenesis throughout lactation at doses that produced maternal exposures up to 7 times the exposure at the recommended clinical dose. In rabbits, eflapegrastim-xnst caused embryofetal lethality and reduced fetal weight when administered during the organogenesis period at approximately 6 times the exposure at the clinical dose (see Data).

The estimated background risk of major birth defects and miscarriage for the indicated population is unknown. All pregnancies have a background risk of birth defect, loss, or other adverse outcomes. In the U.S. general population, the estimated background risks of major birth defects and miscarriage in clinically recognized pregnancies is 2-4% and 15-20%, respectively.

Data

Animal Data

In an embryofetal developmental study in rabbits, eflapegrastim-xnst was administered subcutaneously every other day during the period of organogenesis at doses up to 10 times the clinical exposure at the maximum recommended dose of 13.2 mg. Increased post-implantation loss, reduced number of live fetuses, and reduced fetal body weights were observed at 6 times the clinical exposure, based on AUC. No malformations were observed up to 10 times the clinical exposure, based on AUC.

In an embryofetal developmental study in rats, eflapegrastim-xnst administered subcutaneously every other day during the period of organogenesis did not adversely affect embryofetal development at doses up to 7 times clinical exposure, based on AUC.

In a pre- and post-natal development study in rats, eflapegrastim-xnst administered subcutaneously once weekly from organogenesis through lactation did not adversely affect behavioral, developmental, or reproductive parameters at doses up to 7 times the clinical exposure, based on AUC.

8.2 Lactation

Risk Summary

There are no data on the presence of eflapegrastim-xnst in human milk, the effects on the breastfed child, or the effects on milk production. Endogenous granulocyte colony-stimulating factor (G-CSF) is present in human milk. Other recombinant human granulocyte colony-stimulating factor (rhG-CSF) products are present in human milk at low levels and are not orally absorbed by infants. The developmental and health benefits of breastfeeding should be considered along with the mother’s clinical need for Rolvedon and any potential adverse effects on the breastfed child from Rolvedon or from the underlying maternal condition.

8.4 Pediatric Use

Safety and effectiveness in pediatric patients have not been established.

8.5 Geriatric Use

Of the 314 patients in clinical studies of Rolvedon, 39% were 65 and over, while 6% were 75 and over. No overall differences in safety or effectiveness were observed between these subjects and younger subjects.

10 OVERDOSAGE

Overdose of Rolvedon may result in leukocytosis and bone pain. In the event of overdose, general supportive measures should be instituted as necessary. Monitor the patient for adverse reactions [see Adverse Reactions (6)].

11 DESCRIPTION

Eflapegrastim-xnst is a granulocyte colony-stimulating factor (G‑CSF) produced by covalent coupling of a human G-CSF analog (18.6 kDa) and an Fc fragment of human immunoglobulin G4 (IgG4) (49.8 kDa), both derived from recombinant E. coli, via a single 3.4 kDa polyethylene glycol linker. The recombinant G-CSF domain in eflapegrastim-xnst is a variant of human G-CSF with two serine substitutions at positions 17 and 65, and no additional N-terminal methionine. Eflapegrastim-xnst has a molecular weight of approximately 72 kDa.

Rolvedon (eflapegrastim-xnst) injection is a sterile, preservative-free, clear, colorless solution supplied in a single-dose prefilled syringe for subcutaneous use. Each 0.6 mL single-dose prefilled syringe contains 13.2 mg of eflapegrastim-xnst, citric acid monohydrate (2.52 mg), mannitol (30 mg), polysorbate 80 (0.72 mg) and sodium chloride (5.26 mg) in Water for Injection. Sodium hydroxide may be used to adjust pH to 5.5 during manufacturing.

12 CLINICAL PHARMACOLOGY

12.1 Mechanism of Action

Eflapegrastim-xnst is a recombinant human granulocyte growth factor that binds to G-CSF receptors on myeloid progenitor cells and neutrophils, triggering signaling pathways that control cell differentiation, proliferation, migration and survival.

12.2 Pharmacodynamics

Eflapegrastim-xnst has been shown to elevate neutrophil counts in healthy subjects and in cancer patients. Absolute neutrophil count (ANC), Cmax and area under the effect curve (AUEClast) increased with increasing doses of eflapegrastim-xnst in a linear, but less than dose-proportional, manner over a dose range of 45 to 350 mcg/kg.

12.3 Pharmacokinetics

The pharmacokinetics of eflapegrastim-xnst was studied in healthy subjects and patients with breast cancer. After subcutaneous (SC) dosing, the pharmacokinetics of eflapegrastim-xnst was nonlinear and exposure increases were not dose-proportional over the dose range of 45 to 350 mcg/kg.

Absorption

The median Tmax of eflapegrastim-xnst is 25 hours (6 to 144 hours) in patients with breast cancer following administration of the recommended dosage.

Distribution

The volume of distribution of eflapegrastim-xnst is 1.44 L.

Elimination

The geometric mean half-life of eflapegrastim-xnst in patients with breast cancer is 36.4 hours (Range: 16.1 to 115 hours) during Cycle 1. Eflapegrastim-xnst clearance decreased with increasing doses following single dose administration, suggesting target-mediated clearance of eflapegrastim-xnst by neutrophils. Following repeat administration, clearance increased in Cycle 3 as compared to Cycle 1, potentially due to the subsequent increase in neutrophils. In in vitro studies, the IgG4 Fc fragment in eflapegrastim-xnst binds to the neonatal Fc receptor (FcRn), facilitating the FcRn-mediated transcytosis of eflapegrastim-xnst.

Metabolism

Eflapegrastim-xnst is expected to be metabolized by endogenous degradation following receptor-mediated internalization by cells bearing the G-CSF receptor.

Excretion

Eflapegrastim-xnst was not detected in urine.

Drug Interaction Studies

No studies evaluating the drug interaction potential of eflapegrastim-xnst have been conducted.

12.6 Immunogenicity

The observed incidence of anti-drug antibodies is highly dependent on the sensitivity and specificity of the assay. Differences in assay methods preclude meaningful comparisons of the incidence of anti-drug antibodies in the studies described below with the incidence of anti-drug antibodies in other studies, including those of eflapegrastim-xnst or of other eflapegrastim products.

Antibodies to eflapegrastim-xnst were detected using bridging enzyme-linked immunosorbent assay (ELISA) with a sensitivity of 65 ng/mL. During the 12-week treatment period in the two randomized studies, twenty-one of 297 (7.1%) patients treated with eflapegrastim-xnst developed antibodies. At the 12-month follow-up visit after the last dose of treatment in the two randomized studies, 28 of 297 (9.4%) patients treated with eflapegrastim-xnst developed antibodies.

Neutralizing antibodies were detected by a cell-based assay with a sensitivity of 1.95 mcg/mL. One patient out of 297 (0.3%) in the eflapegrastim-xnst arm tested positive for neutralizing antibodies post-treatment. Treatment-emergent anti-PEG antibodies were detected by a direct binding ELISA in 126 out of 268 patients (47%) treated with eflapegrastim-xnst. There was no identified clinically significant effect of anti-drug antibodies on pharmacokinetics, pharmacodynamics, safety or effectiveness of Rolvedon over the treatment duration of 12 weeks. There was no identified clinically significant effect of anti-drug antibodies on the safety profile of Rolvedon during the 12-month follow-up period after the last dose.

13 NONCLINICAL TOXICOLOGY

13.1 Carcinogenesis, Mutagenesis, Impairment of Fertility

No long-term carcinogenicity studies have been performed with eflapegrastim-xnst.

Eflapegrastim-xnst was not mutagenic or clastogenic in a standard battery of genotoxicity tests (bacterial mutagenicity (Ames), Chinese hamster ovary cells chromosomal aberration, rat bone marrow micronucleus).

Eflapegrastim-xnst did not affect reproductive performance or fertility in male or female rats at weekly doses up to 7 times the clinical exposure at the maximum recommended dose of 13.2 mg.

14 CLINICAL STUDIES

Patients with Cancer Receiving Myelosuppressive Chemotherapy

The efficacy of Rolvedon to decrease the incidence of infection, as manifested by febrile neutropenia, in patients with nonmyeloid malignancies receiving myelosuppressive anti-cancer drugs was evaluated in two 1:1 randomized, open-label, active-controlled non-inferiority studies of similar design (Study 1 [NCT02643420] and Study 2 [NCT02953340]) that enrolled a total of 643 patients with early-stage breast cancer. Docetaxel 75 mg/m] and Study 2 [NCT02953340]) that enrolled a total of 643 patients with early-stage breast cancer. Docetaxel 75 mg/m^2 and cyclophosphamide 600 mg/m^2 (TC) were administered intravenously every 21 days (on Day 1 of each cycle) for up to 4 cycles. A fixed dose of Rolvedon 13.2 mg/0.6 mL or pegfilgrastim (6 mg/0.6 mL) was administered subcutaneously on Day 2 of each cycle after TC chemotherapy.

The median age of patients enrolled in the two randomized studies was 60 years (Range: 24 to 88), the majority of patients were female (>99%), 77% were White and 12% were Black or African American.

Study 1 enrolled 406 patients; 196 patients to the Rolvedon arm and 210 patients to the pegfilgrastim arm. Study 2 enrolled 237 patients; 118 patients to the Rolvedon arm and 119 patients to the pegfilgrastim arm. Efficacy for both trials was based on the duration of severe neutropenia (DSN) in Cycle 1.

Efficacy results are shown in Table 2. In both studies, Rolvedon was non-inferior to pegfilgrastim. The distributions of the severe neutropenia events in percentage from Cycle 1 for Study 1 and Study 2 are presented in Figure 1.

Table 2. Duration of Severe Neutropenia (DSN) in Cycle 1 (Study 1 and Study 2)
 | Study 1 |  | Study 2
 | Rolvedon; (n=196) | Pegfilgrastim; (n=210) | Rolvedon; (n=118) | Pegfilgrastim; (n=119)
Mean DSN (SD) (Days) | 0.20 (0.503) | 0.35 (0.683) | 0.31 (0.688) | 0.39 (0.949)
Median DSN (Range) (Days) | 0 (0, 3) | 0 (0, 3) | 0 (0, 3) | 0 (0, 7)
Difference in DSN (Days) | -0.148 |  | -0.073
*95% Confidence Intervala | -0.265, -0.033 |  | -0.292, 0.129
aConfidence intervals were obtained using 2.5 percentile and 97.5 percentile of the 100,000 bootstrap samples with treatment as stratification factor.
*The non-inferiority of Rolvedon to pegfilgrastim was to be declared if the upper bound of 95% CI of the difference in mean DSN between the treatment arms was <0.62 days.

Figure 1. Duration of Severe Neutropenia (DSN) by Day in Cycle 1 (Study 1 and Study 2)

16 HOW SUPPLIED/STORAGE AND HANDLING

Rolvedon (eflapegrastim-xnst) injection is a clear, colorless solution supplied in a single-dose prefilled syringe containing 13.2 mg of eflapegrastim-xnst in 0.6 mL solution, with 29-gauge 1/2 inch pre-attached (staked) needle with a needle guard.

Rolvedon is provided in a dispensing pack containing one sterile 13.2 mg/0.6 mL prefilled syringe (NDC 82497-132-01).

Store refrigerated at 36°F to 46°F (2°C to 8°C) in the carton to protect from light. Do not shake. Discard any prefilled syringe left at room temperature for greater than 72 hours. Do not freeze; discard syringe if frozen.

17 PATIENT COUNSELING INFORMATION

Advise the patient to read the FDA-approved patient labeling (Patient Information and Instructions for Use). Inform patients to contact their healthcare provider with any questions.

Advise patients of the following risks and potential risks with Rolvedon:

•Splenic rupture and splenomegaly [see Warnings and Precautions (5.1)]

•Acute respiratory distress syndrome [see Warnings and Precautions (5.2)]

•Serious allergic reactions [see Warnings and Precautions (5.3)]

•Sickle cell crisis [see Warnings and Precautions (5.4)]

•Glomerulonephritis [see Warnings and Precautions (5.5)]

•Leukocytosis [see Warnings and Precautions (5.6)]

•Thrombocytopenia [see Warnings and Precautions (5.7)]

•Capillary leak syndrome [see Warnings and Precautions (5.8)]

•Potential for tumor growth stimulatory effects on malignant cells [see Warnings and Precautions (5.9)]

•Increased risk of myelodysplastic syndrome and/or acute myeloid leukemia in patients with breast and lung cancer who receive Rolvedon in conjunction with chemotherapy and/or radiation therapy [see Warnings and Precautions (5.10)]

•Aortitis [see Warnings and Precautions (5.11)]

Instruct patients who self-administer Rolvedon using the single-dose prefilled syringe of the:

•Importance of following the Instructions for Use

•Dangers of reusing syringes

•Importance of following local requirements for proper disposal of used syringes.

Manufactured by:
Assertio Specialty Pharmaceuticals, LLC
Lake Forest, IL 60045

U.S. License No. 2428

PATIENT INFORMATION

ROLVEDON® (roll veh don)

(eflapegrastim-xnst)

injection

What is Rolvedon?

Rolvedon is a man-made form of granulocyte colony-stimulating factor (G-CSF). G-CSF is a substance produced by the body. It stimulates the growth of neutrophils, a type of white blood cell important in the body’s fight against infection.

It is not known if Rolvedon is safe and effective in children.

Do not take Rolvedon if you have had a serious allergic reaction to eflapegrastim, pegfilgrastim or filgrastim products.

Before receiving Rolvedon, tell your healthcare provider about all of your medical conditions, including if you:

• have a sickle cell disorder

• have kidney problems

• are pregnant or plan to become pregnant. It is not known if Rolvedon can harm your unborn baby. Tell your healthcare provider right away if you become pregnant during treatment with Rolvedon.

• are breastfeeding or plan to breastfeed. It is not known if Rolvedon passes into your breast milk.

Tell your healthcare provider about all the medicines you take, including prescription and over-the-counter medicines, vitamins, and herbal supplements.

How will I receive Rolvedon?

• Rolvedon is given as an injection under your skin (subcutaneous injection) by a healthcare provider. If your healthcare provider decides that the subcutaneous injections can be given at home by you or your caregiver, follow the detailed “Instructions for Use” that comes with your Rolvedon for information on how to prepare and inject a dose of Rolvedon.

• You and your caregiver will be shown how to prepare and inject Rolvedon before you use it.

• You will receive 1 injection of Rolvedon for each cycle of chemotherapy.

• You will receive your injection of Rolvedon about 24 hours after you finish receiving your chemotherapy.

• You should not receive Rolvedon for 14 days before or within 24 hours after your dose of chemotherapy.

• If you miss a dose of Rolvedon, talk to your healthcare provider about when you should receive your next dose.

What are the possible side effects of Rolvedon?

Rolvedon may cause serious side effects, including:

• Spleen rupture. Your spleen may become enlarged and can rupture. A ruptured spleen can cause death. Call your healthcare provider right away if you have pain in the left upper stomach-area or your left shoulder.

• A serious lung problem called Acute Respiratory Distress Syndrome (ARDS). Call your healthcare provider or get emergency help right away if you have shortness of breath with or without a fever, trouble breathing, or a fast rate of breathing.

• Serious allergic reactions. Rolvedon can cause serious allergic reactions. These reactions can cause a rash all over your whole body, shortness of breath, wheezing, dizziness, swelling around your mouth or eyes, fast heart rate, and sweating. If you have any of these symptoms, stop using Rolvedon and call your healthcare provider or get emergency medical help right away.

• Sickle cell crises. You may have a serious sickle cell crisis, which could lead to death, if you have a sickle cell disorder and receive Rolvedon. Call your healthcare provider right away if you develop symptoms of sickle cell crisis such as pain or difficulty breathing.

• Kidney injury (glomerulonephritis). Rolvedon can cause kidney injury. Call your healthcare provider right away if you develop any of the following symptoms:

o swelling of your face or ankles

o blood in your urine or dark colored urine

o you urinate less than usual

• Increased white blood cell count (leukocytosis). Your healthcare provider will check your blood count during treatment with Rolvedon.

• Decreased platelet count (thrombocytopenia). Your healthcare provider will check your blood during treatment with Rolvedon. Tell your healthcare provider if you have unusual bleeding or bruising during treatment with Rolvedon. This could be a sign of decreased platelet counts, which may reduce the ability of your blood to clot.

• Capillary Leak Syndrome. Rolvedon can cause fluid to leak from blood vessels into your body’s tissues. This condition is called “Capillary Leak Syndrome” (CLS). CLS can quickly cause you to have symptoms that may become life-threatening. Get emergency help right away if you develop any of the following symptoms:

o swelling or puffiness and are urinating less than usual

o trouble breathing

o swelling of your stomach area (abdomen) and feeling of fullness

o dizziness or feeling faint

o a general feeling of tiredness

• Myelodysplastic syndrome and acute myeloid leukemia. If you have breast cancer or lung cancer, when Rolvedon is used with chemotherapy and radiation therapy, or with radiation therapy alone, you may have an increased risk of developing a precancerous blood condition called myelodysplastic syndrome (MDS) or a blood cancer called acute myeloid leukemia (AML). Symptoms of MDS and AML may include tiredness, fever, and easy bruising or bleeding. Call your healthcare provider if you develop these symptoms during treatment with Rolvedon.

• Inflammation of the aorta (aortitis). Inflammation of the aorta (the large blood vessel which transports blood from the heart to the body) has been reported in patients who received pegfilgrastim products. Symptoms may include fever, abdominal pain, feeling tired, and back pain. Call your healthcare provider if you experience these symptoms.

The most common side effects of Rolvedon include:

• tiredness

• nausea

• diarrhea

• bone pain

• headache

• fever

• decreased red blood cell count

• rash

• muscle and joint pain

• back pain

These are not all the possible side effects of Rolvedon.

Call your doctor for medical advice about side effects. You may report side effects to FDA at 1-800-FDA-1088.

How should I store Rolvedon?

• Store Rolvedon in the refrigerator between 36°F to 46°F (2°C to 8°C).

• Do not freeze Rolvedon. Throw away (dispose of) any Rolvedon that has been frozen.

• Store Rolvedon in the original carton to protect from light.

• Do not shake Rolvedon.

• Take the carton out of the refrigerator and place the sealed blister tray on a clean flat surface for at least 30 minutes to allow it to reach room temperature before use.

• Throw away (dispose of) any prefilled syringe of Rolvedon that has been left at room temperature, 68ºF to 77ºF (20ºC to 25ºC), for more than 72 hours.

Keep Rolvedon and all medicines out of the reach of children.

General information about the safe and effective use of Rolvedon.

Medicines are sometimes prescribed for purposes other than those listed in a Patient Information leaflet. Do not use Rolvedon for a condition for which it was not prescribed. Do not give Rolvedon to other people, even if they have the same symptom that you have. It may harm them. You can ask your pharmacist or healthcare provider for information about Rolvedon that is written for health professionals.

What are the ingredients in Rolvedon?

Active ingredient: eflapegrastim-xnst

Inactive ingredients: citric acid monohydrate, mannitol, polysorbate 80, and sodium chloride in Water for Injection. Sodium hydroxide may be used to adjust pH to 5.5 during manufacturing.

Manufactured by: Assertio Specialty Pharmaceuticals, LLC, Lake Forest, IL 60045

U.S. License No. 2428

For more information, go to www.rolvedon.com or call 1-800-518-1084.

This Patient Information has been approved by the U.S. Food and Drug Administration.

Revised: 02/2026

INSTRUCTIONS FOR USE

ROLVEDON® [roll veh don]

(eflapegrastim-xnst)

injection, for subcutaneous use

Single-Dose Preﬁlled Syringe

This Instructions for Use contains information on how to inject Rolvedon. Read this Instructions for Use before using Rolvedon and each time you get a refill. There may be new information. This information does not take the place of talking to your healthcare provider about your medical condition or treatment.

Important Information You Need To Know Before Injecting Rolvedon

• It is important that you do not try to give the injection unless you or your caregiver have received training from your healthcare provider.

• Rolvedon is for use under the skin (subcutaneous injection) only.

• To help reduce needle stick injuries, each preﬁlled syringe has a needle guard that is automatically activated to cover the needle after the injection is complete.

• Make sure the name Rolvedon appears on the carton and prefilled syringe label.

• Do not use a Rolvedon prefilled syringe after the expiration date on the label.

• Do not use the Rolvedon prefilled syringe if it has been dropped on a hard surface. The prefilled syringe may be broken even if you cannot see the break. Use a new prefilled syringe.

• Do not use the Rolvedon prefilled syringe if the seal on the carton or the seal on the blister tray is broken.

• Do not shake the Rolvedon prefilled syringe.

• Do not touch the needle guard clips before use. Touching them may cause the needle guard to be activated too early.

• Do not remove the needle cap until just before you give the injection.

Rolvedon prefilled syringe parts

Figure A

Storing the Rolvedon prefilled syringe

• Store Rolvedon in the refrigerator between 36°F to 46°F (2°C to 8°C).

• Do not freeze Rolvedon. Throw away (dispose of) any Rolvedon that has been frozen.

• Store Rolvedon in the original carton to protect from light.

• Take the carton out of the refrigerator and place the sealed blister tray on a clean flat surface for at least 30 minutes to allow it to reach room temperature before use.

• Throw away (dispose of) any prefilled syringe of Rolvedon that has been left at room temperature, 68ºF to 77ºF (20ºC to 25ºC), for more than 72 hours.

Keep Rolvedon and all medicines out of the reach of children.

Preparing to inject Rolvedon

Step 1. Remove the carton from refrigerator

• Remove the carton from the refrigerator (see Figure B).

• Check the expiration date on the carton (see Figure C).

Do not use the prefilled syringe if it is expired or if the carton has been previously opened.

• Open the carton and remove the blister tray.

Figure B

Figure C

Step 2. Allow Rolvedon to reach room temperature

Place the sealed blister tray on a clean flat surface and wait 30 minutes to reach room temperature (see Figure D). Do not warm up the prefilled syringe in any other way.

Figure D

Step 3. Gather the supplies needed for your injection

Gather the following supplies for the injection (see Figure E):

• 1 sterile cotton ball or gauze pad

• 1 alcohol wipe

• 1 sharps disposal container. See “Disposing of used Rolvedon prefilled syringes” at the end of this Instructions for Use.

Figure E

Step 4. Wash your hands

Wash your hands with soap and water.

Step 5. Remove the prefilled syringe from the blister tray

• Open the tray by peeling away the tray cover.

• To remove the prefilled syringe, grip the prefilled syringe by the center of the viewing window as shown in Figure F.

• Do not remove the prefilled syringe by the plunger rod, plunger head, or the needle cap.

• Do not touch the needle guard clips, as it could activate the needle guard.

• Do not remove the needle cap until you are ready to inject.

Figure F

Step 6. Inspect the prefilled syringe and medicine

• Visually inspect the prefilled syringe. Do not use the prefilled syringe if it appears damaged (for example, if the syringe is cracked or broken, or if the plunger rod is detached or broken) or if the needle cap is missing.

• Check the expiration date on the prefilled syringe label. Do not use if the expiration date has passed.

• Check the medicine inside the prefilled syringe through the viewing window (see Figure G). The medicine inside should be clear and colorless. It is normal to see small air bubbles in the medicine. It does not need to be removed.

• Do not use the prefilled syringe if:

o the medicine appears discolored or cloudy.

o the medicine contains lumps, flakes, or particles.

Figure G

Step 7. Select the injection site

Figure H

•The recommended injection sites for a subcutaneous injection are the (see Figure H):

o Abdomen (except for a two-inch area surrounding the navel)

o Upper outer thighoOuter upper arm (only if someone else is giving you the injection)

o Upper outer buttock (only if someone else is giving you the injection)

• Do not inject into area of the skin that is tender, damaged, bruised, scarred or hard.

• Do not inject into moles, scars, birthmarks or stretchmarks.

• If you want to use the same injection site, make sure it is not the same spot on the injection site you used for a previous injection.

Step 8. Clean the injection site

• Clean the injection site with an alcohol wipe (see Figure I). • Allow the area of skin to dry before injecting.

Do not touch or blow on the cleaned area before injecting.

Figure I

Injecting Rolvedon

Step 9. Remove needle cap

• Do not remove the needle cap until you are ready to inject. When ready for the injection, carefully remove the needle cap by pulling it straight off (see Figure J).

• When removing the needle cap, hold the prefilled syringe as shown in Figure J.

• Throw away (dispose of) the needle cap in the sharps disposal container.

• Do not put the needle cap back onto the prefilled syringe after it has been removed. This can damage the needle and cause needle stick injuries.

• Do not hold the prefilled syringe by the plunger rod or touch the needle guard clips when removing the needle cap.

Figure J

Step 10. Insert the needle

• Hold the prefilled syringe at a 45 to 90-degree angle (see Figure K).

• Using your other hand, gently pinch the cleaned injection site as shown in Figure K.

• Fully insert the needle into the skin in a quick “dart-like” motion.

Do not touch the plunger head while inserting the needle into the skin.

Figure K

Step 11. Inject Rolvedon

• Release the pinched skin.

• Hold the prefilled syringe as shown in Figure L with your thumb on the plunger head ready to inject.

• Slowly press the plunger head down to inject the medicine.

• Hold the syringe steadily in place while the needle is inserted.

Note: You may feel some resistance, this is normal.

Figure L

• Push the plunger head down until it reaches the bottom to make sure all of the medicine is injected (see Figure M).

• You may hear a click when the plunger head reaches the bottom.

Figure M

Step 12. Activate the needle guard

• Gently lift your thumb to release the plunger until the entire needle is covered by the needle guard. Then remove the prefilled syringe from the injection site at the same angle as inserted as shown in Figure N.

• If there is bleeding, lightly press a cotton ball or gauze on the injection site.

Figure N

Disposing of used Rolvedon prefilled syringes

• Put the used prefilled syringe and needle cap in an FDA-cleared sharps disposal container right away after use (see Figure O). Do not throw away (dispose of) the prefilled syringe in your household trash.

• If you do not have an FDA-cleared sharps disposal container, you may use a household container that is:

o made of a heavy-duty plastic,

o can be closed with a tight-fitting, puncture-resistant lid, without sharps being able to come out,

o upright and stable during use,

o leak-resistant, and

o properly labeled to warn of hazardous waste inside the container.

• When your sharps disposal container is almost full, you will need to follow your community guidelines for the right way to dispose of your sharps disposal container. There may be state or local laws about how you should throw away used needles and syringes. For more information about safe sharps disposal, and for specific information about sharps disposal in the state that you live in, go to the FDA’s website at: http://www.fda.gov/safesharpsdisposal.

• Do not reuse the prefilled syringes or throw them into household waste.

• Do not recycle prefilled syringes or sharps disposal container.

• Do notattempt to remove the needle from the prefilled syringe.

Important: Keep the sharps disposal container out of the reach of children.

Figure O

Manufactured by: Assertio Specialty Pharmaceuticals, LLC Lake Forest, IL 60045

U.S. License No. 2428

For more information, go to www.rolvedon.com or call 1-800-518-1084.

This Instructions for Use has been approved by the U.S. Food and Drug Administration. Issued: 02/2026

PACKAGE/LABEL PRINCIPAL DISPLAY PANEL

Rolvedon

(eflapegrastim-xnst)

injection

13.2 mg/0.6 mL

Rolvedon

(eflapegrastim-xnst)

injection

13.2 mg/0.6 mL

For subcutaneous injection

Sterile Solution – No Preservative

One 0.6 mL Single-dose Pre-filled Syringe

Rolvedon

(eflapegrastim-xnst)

injection

13.2 mg/0.6 mL

NDC 82497-132-01

Rx only

For subcutaneous injection

Sterile Solution – No Preservative

One 0.6 mL Single-dose Pre-filled Syringe